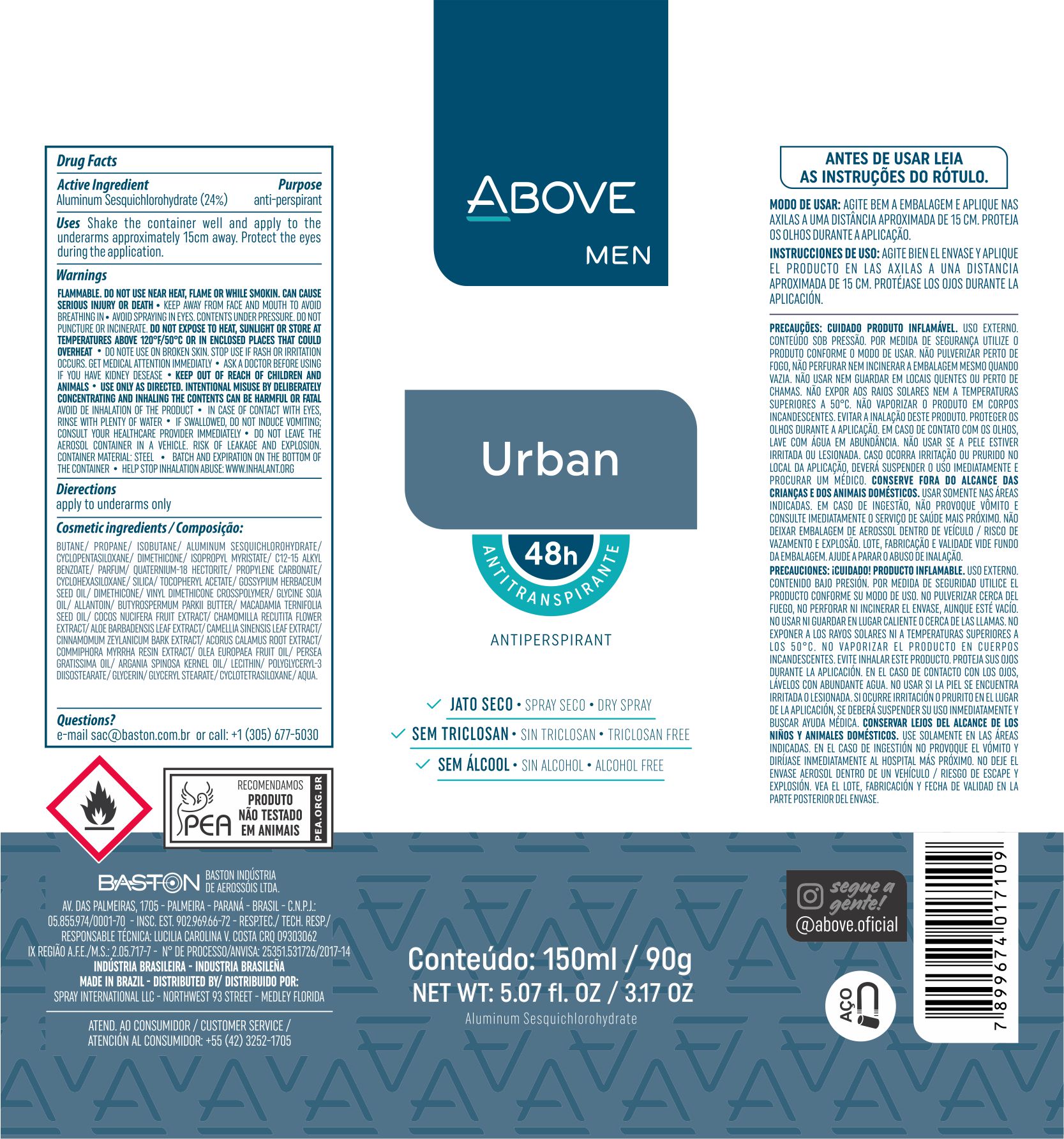 DRUG LABEL: Antiperspirant Above Urban
NDC: 73306-1106 | Form: AEROSOL, SPRAY
Manufacturer: Baston Industria de Aerossóis Ltda
Category: otc | Type: HUMAN OTC DRUG LABEL
Date: 20241226

ACTIVE INGREDIENTS: ALUMINUM SESQUICHLOROHYDRATE 24 g/100 g
INACTIVE INGREDIENTS: PROPYLENE CARBONATE; POLYGLYCERYL-3 DIISOSTEARATE; ACORUS CALAMUS ROOT; ALOE VERA LEAF; LEVANT COTTON SEED; .ALPHA.-TOCOPHEROL ACETATE; GLYCERIN; DIMETHICONE; ARGAN OIL; COCONUT; SILICA DIMETHYL SILYLATE; PROPANE; DISTEARDIMONIUM HECTORITE; AVOCADO OIL; CYCLOMETHICONE 5; VINYL DIMETHICONE/METHICONE SILSESQUIOXANE CROSSPOLYMER; WATER; ISOPROPYL MYRISTATE; GREEN TEA LEAF; CINNAMON BARK OIL; MACADAMIA OIL; BUTANE; ALLANTOIN; CHAMOMILE; ISOBUTANE; GLYCERYL MONOSTEARATE; LECITHIN, SOYBEAN; SHEA BUTTER; MYRRH OIL

Antiperspirant Above Urban